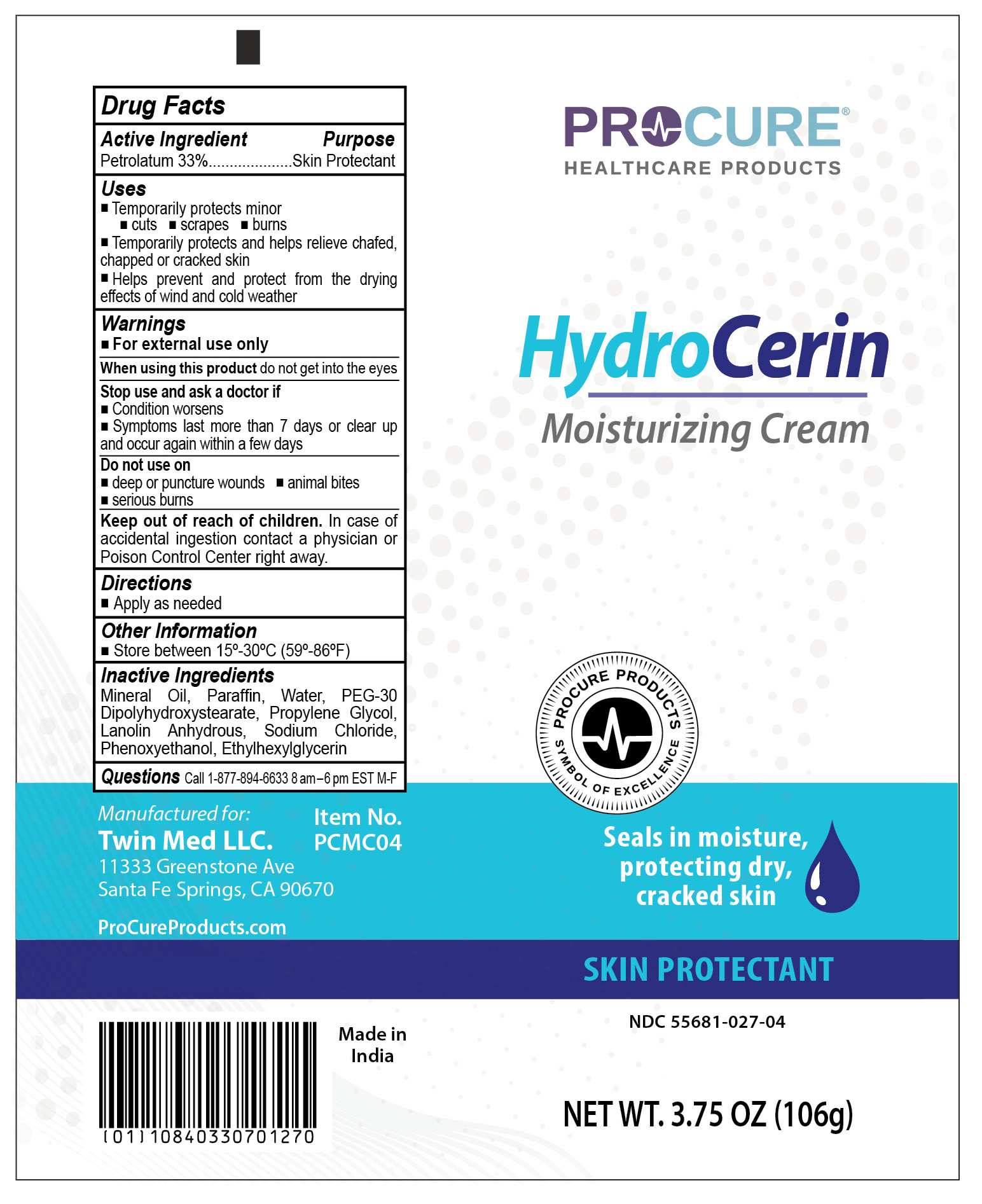 DRUG LABEL: ProCure HydroCerin
NDC: 55681-027 | Form: CREAM
Manufacturer: Twin Med LLC
Category: otc | Type: HUMAN OTC DRUG LABEL
Date: 20250724

ACTIVE INGREDIENTS: PETROLATUM 33 g/100 g
INACTIVE INGREDIENTS: PHENOXYETHANOL; SODIUM CHLORIDE; PARAFFIN; WATER; ETHYLHEXYLGLYCERIN; PEG-30 DIPOLYHYDROXYSTEARATE; PROPYLENE GLYCOL; MINERAL OIL; LANOLIN

Active Ingredient

Active Ingredient: Petrolatum 33%

Purpose

Purpose: Skin Protectant

Uses

- Temporarily protects minor: cuts, scrapes, and burns
- Temporarily protects and helps relieve chafed, chapped or cracked skin
- Helps prevent and protect from the drying effects of wind and cold weather

Warnings

For external use only

When using this product do not get into the eyes

Stop use and ask a doctor if

- Condition worsens
- Symptoms last more than 7 days or clear up and occur again within a few days

Do not use on deep or puncture wounds, animal bites, serious burns

Keep out of reach of children. In case of accidental ingestion contact a physician or Poison Control Center right away.

Directions

Apply as needed

Inactive Ingredients

Mineral Oil, Paraffin, Water, PEG-30 Dipolyhydroxystearate, Propylene Glycol, Lanolin Anhydrous, Sodium Chloride, Phenoxyethanol, Ethylhexylglycerin